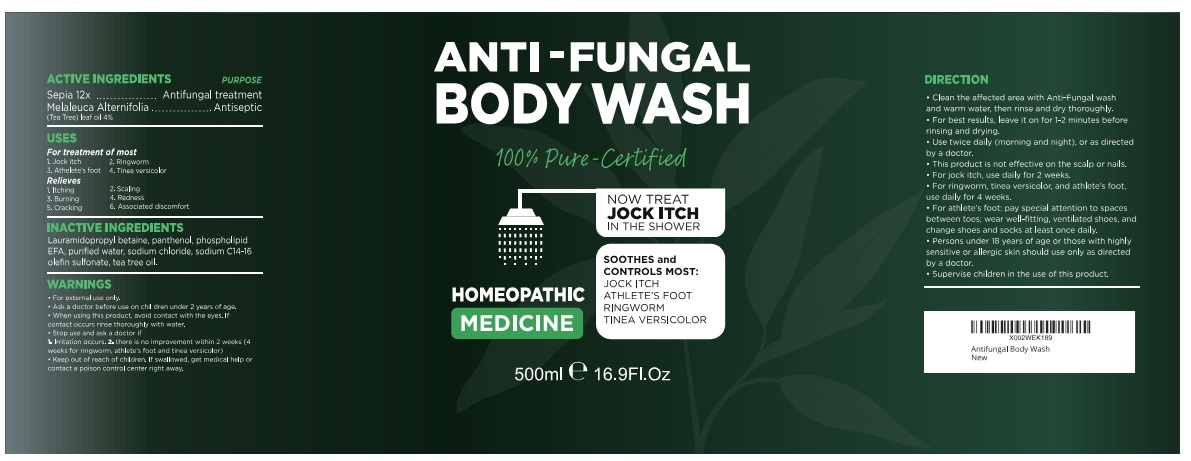 DRUG LABEL: Anti Fungal Foot and Body
NDC: 83004-011 | Form: LIQUID
Manufacturer: Rida LLC
Category: homeopathic | Type: HUMAN OTC DRUG LABEL
Date: 20251006

ACTIVE INGREDIENTS: SEPIA OFFICINALIS JUICE 12 [hp_X]/1 mL; TEA TREE OIL 0.04 g/1 mL
INACTIVE INGREDIENTS: PANTHENOL; WATER; SODIUM CHLORIDE; SODIUM C14-16 OLEFIN SULFONATE; LAURAMIDOPROPYL BETAINE

Active ingredient Purpose

SEPIA OFFICINALIS JUICE Antifungal treatment

melaleuca alternifolia (Tea Antifungal treatment
Tree) Leaf Oil

Uses

For the treatment of most
● jock itch (tinea cruris)
● ringworm (tinea corporis)
● athlete's foot (tinea pedis)
● tinea versicolor

For relief of:
● itching
● scaling
● cracking
● burning
● irritation

Warnings

For external use only

Ask a doctor before use onchildren under 2 years of age.

When using this productavoid contact with the eyes. If contact occurs rinse thoroughly with water.

Stop use and ask a doctor if
● irritation occurs
● there is no improvement within 2 weeks (4 weeks for ringworm, athlete&#39;s foot and
tinea versicolor).

Keep out of reach of children.If swallowed, get medical help or contact a Poison Control Center right away.

DIRECTIONS

- Read all package directions and warnings before use.
- Use only as directed.
- Clean the affected area with Anti-Fungal Wash and warm water, rinse and dry thoroughly.
- For best results, leave on for 1-2 minutes before rinsing and drying.
- Use twice daily (morning and night), or as directed by a doctor.
- This product is not effective on scalp or nails.
- For jock itch, use daily for 2 weeks.
- For ringworm, tinea versicolor and athlete&#39;s foot, use daily for 4 weeks. If condition persists longer, consult a doctor.
- For athlete&#39;s foot: pay special attention to spaces between the toes; wear well-fitting,ventilated shoes, and change shoes and socks at least once daily.
- Intended for use by normally healthy adults only.
- Persons under 18 years of age or those with highly sensitive or allergic skin should use only as directed by a doctor.
- Supervise children in the use of this product.

Inactive Ingredients

Lauramidopropyl betaine, panthenol, phospholipid EFA, purified water, sodium chloride, sodium C14 - 16 olefin sulfonate, tea tree oil.